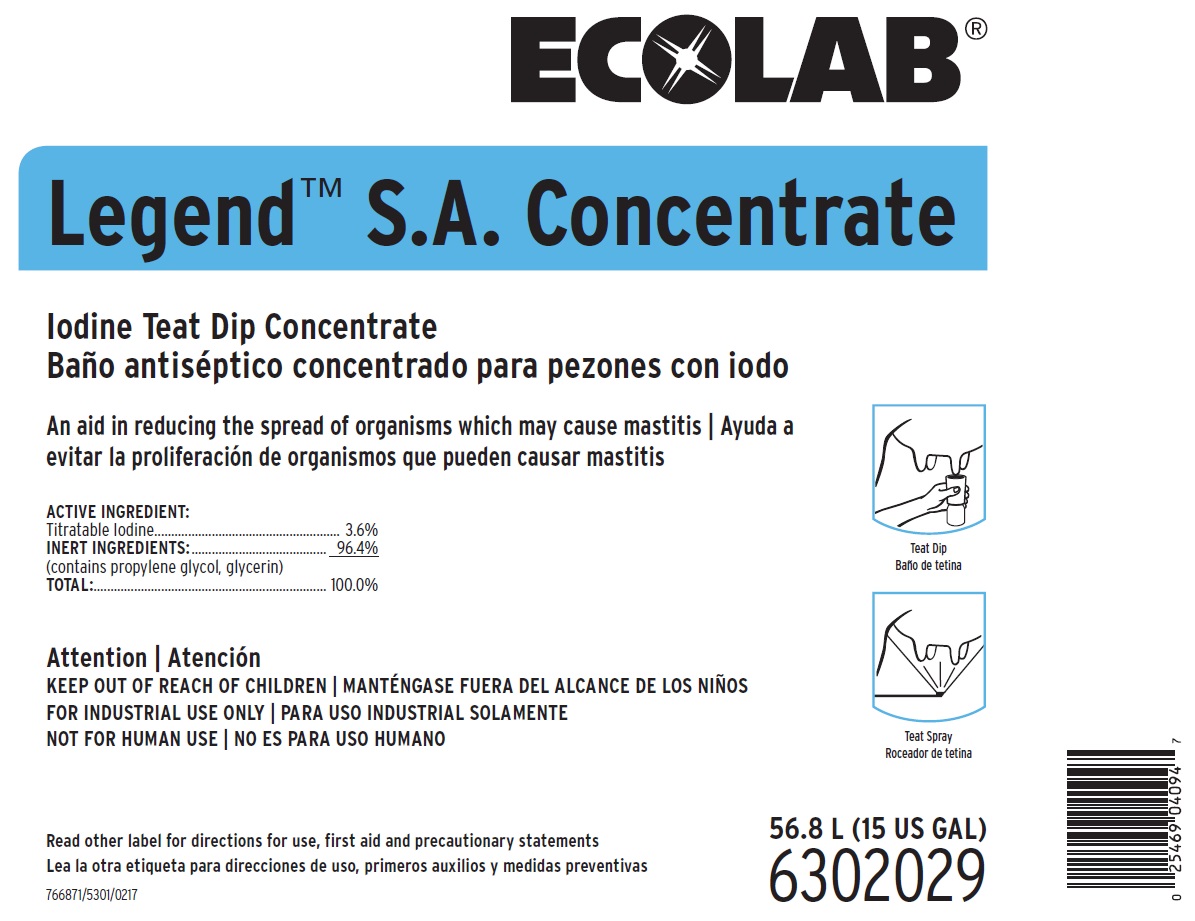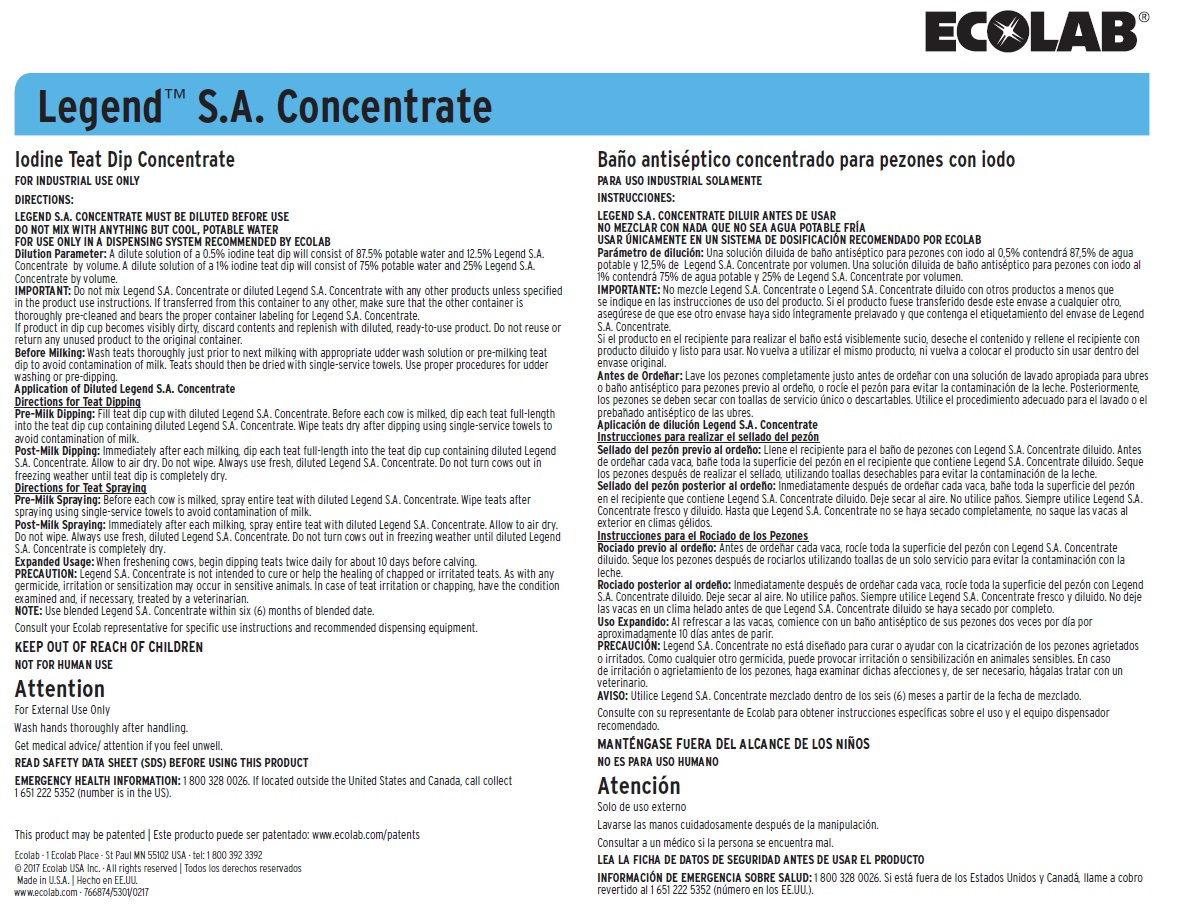 DRUG LABEL: Legend S.A.
NDC: 47593-574 | Form: SOLUTION
Manufacturer: Ecolab Inc.
Category: animal | Type: OTC ANIMAL DRUG LABEL
Date: 20251012

ACTIVE INGREDIENTS: IODINE 36 mg/1 mL
INACTIVE INGREDIENTS: GLYCERIN; PROPYLENE GLYCOL; WATER

SAFE HANDLING WARNING

NOT FOR HUMAN USE

Attention

For External Use Only

Wash hands thoroughly after handling.

Get medical advice/ attention if you feel unwell.

READ SAFETY DATA SHEET (SDS) BEFORE USING THIS PRODUCT

EMERGENCY HEALTH INFORMATION: 1 800 328 0026. If located outside the United States and Canada, call collect

DIRECTIONS:

LEGEND S.A. CONCENTRATE MUST BE DILUTED BEFORE USE

DO NOT MIX WITH ANYTHING BUT COOL, POTABLE WATER

FOR USE ONLY IN A DISPENSING SYSTEM RECOMMENDED BY ECOLAB

Dilution Parameter: A dilute solution of a 0.5% iodine teat dip will consist of 87.5% potable water and 12.5% Legend S.A. Concentrate by volume. A dilute solution of a 1% iodine teat dip will consist of 75% potable water and 25% Legend S.A. Concentrate by volume.

IMPORTANT: Do not mix Legend S.A. Concentrate or diluted Legend S.A. Concentrate with any other products unless specified in the product use instructions. If transferred from this container to any other, make sure that the other container is thoroughly pre-cleaned and bears the proper container labeling for Legend S.A. Concentrate.

If product in dip cup becomes visibly dirty, discard contents and replenish with diluted, ready-to-use product. Do not reuse or return any unused product to the original container.

Before Milking: Wash teats thoroughly just prior to next milking with appropriate udder wash solution or pre-milking teat dip to avoid contamination of milk. Teats should then be dried with single-service towels. Use proper procedures for udder washing or pre-dipping.

Application of Diluted Legend S.A. Concentrate

Directions for Teat Dipping

Pre-Milk Dipping: Fill teat dip cup with diluted Legend S.A. Concentrate. Before each cow is milked, dip each teat full-length into the teat dip cup containing diluted Legend S.A. Concentrate. Wipe teats dry after dipping using single-service towels to avoid contamination of milk.

Post-Milk Dipping: Immediately after each milking, dip each teat full-length into the teat dip cup containing diluted Legend S.A. Concentrate. Allow to air dry. Do not wipe. Always use fresh, diluted Legend S.A. Concentrate. Do not turn cows out in freezing weather until teat dip is completely dry.

Directions for Teat Spraying

Pre-Milk Spraying: Before each cow is milked, spray entire teat with diluted Legend S.A. Concentrate. Wipe teats after spraying using single-service towels to avoid contamination of milk.

Post-Milk Spraying: Immediately after each milking, spray entire teat with diluted Legend S.A. Concentrate. Allow to air dry. Do not wipe. Always use fresh, diluted Legend S.A. Concentrate. Do not turn cows out in freezing weather until diluted Legend S.A. Concentrate is completely dry.

Expanded Usage: When freshening cows, begin dipping teats twice daily for about 10 days before calving.

PRECAUTION: Legend S.A. Concentrate is not intended to cure or help the healing of chapped or irritated teats. As with any germicide, irritation or sensitization may occur in sensitive animals. In case of teat irritation or chapping, have the condition examined and, if necessary, treated by a veterinarian.

NOTE: Use blended Legend S.A. Concentrate within six (6) months of blended date.

Consult your Ecolab representative for specific use instructions and recommended dispensing equipment.

KEEP OUT OF REACH OF CHILDREN

FOR INDUSTRIAL USE ONLY

NOT FOR HUMAN USE

Read other label for directions for use, first aid and precautionary statements

Principal Display panel and representative label

Legend™ S.A. Concentrate

Iodine Teat Dip Concentrate

An aid in reducing the spread of organisms which may cause mastitis

ACTIVE INGREDIENT:

Titratable Iodine........................................................ 3.6%

INERT INGREDIENTS:......................................... 96.4%

(contains propylene glycol, glycerin)

TOTAL:..................................................................... 100.0%

Attention | Atención

KEEP OUT OF REACH OF CHILDREN

FOR INDUSTRIAL USE ONLY

NOT FOR HUMAN USE

Read other label for directions for use, first aid and precautionary statements

766871/5301/0217

56.8 L (15 US GAL)

6302029